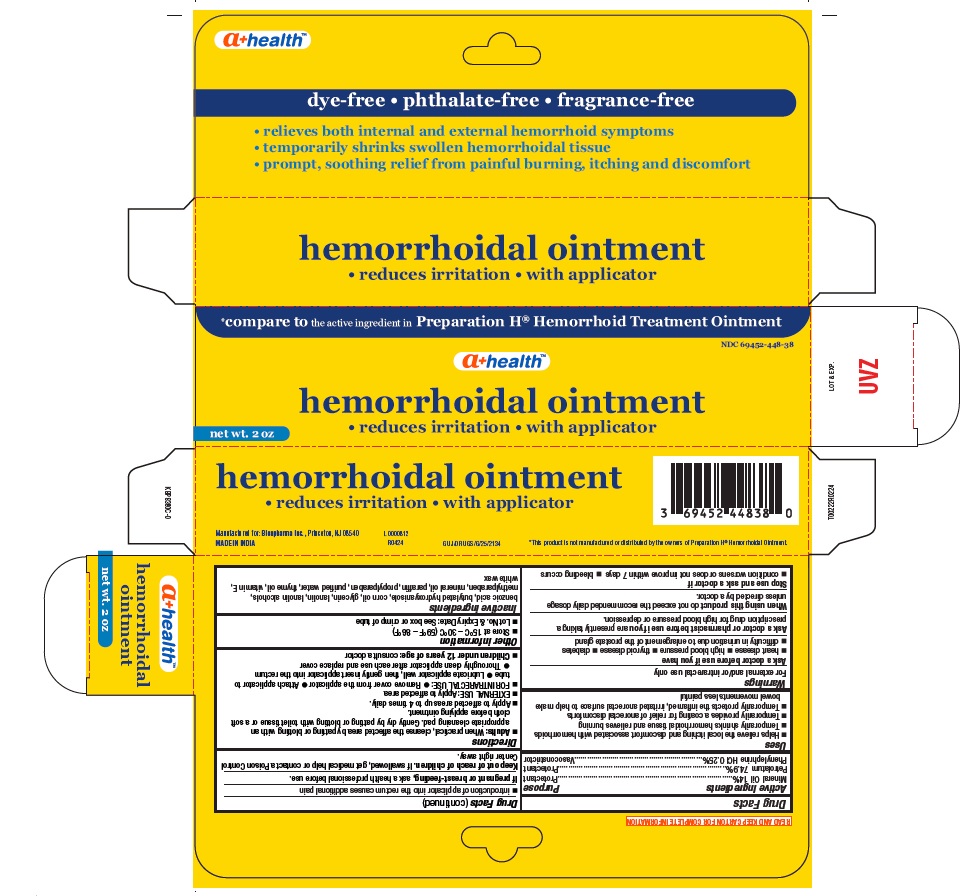 DRUG LABEL: hemorrhoidal
NDC: 69452-448 | Form: OINTMENT
Manufacturer: Bionpharma Inc.
Category: otc | Type: HUMAN OTC DRUG LABEL
Date: 20250331

ACTIVE INGREDIENTS: PETROLATUM 749 mg/1 g; PHENYLEPHRINE HYDROCHLORIDE 2.5 mg/1 g; MINERAL OIL 140 mg/1 g
INACTIVE INGREDIENTS: .ALPHA.-TOCOPHEROL ACETATE; WHITE WAX; BENZOIC ACID; BUTYLATED HYDROXYANISOLE; CORN OIL; LANOLIN; GLYCERIN; LANOLIN ALCOHOLS; METHYLPARABEN; WATER; PARAFFIN; PROPYLPARABEN; THYME OIL

hemorrhoidal, A+ Health

Active ingredient

Mineral Oil 14%

Petrolatum 74.9%

Phenylephrine HCI 0.25%

Purpose

Protectant

Protectant

Vasoconstrictor

Uses

■ Helps relieve the local itching and discomfort associated with hemorrhoids
■ Temporarily shrinks hemorrhoidal tissue and relieves burning
■ Temporarily provides a coating for relief of anorectal discomforts
■ Temporarily protects the inflamed, irritated anorectal surface to help make bowel movements less painful

Warnings

For external and/or intrarectal use only

Ask a doctor before use if you have

■ heart disease ■ high blood pressure ■ thyroid disease ■ diabetes
■ difficulty in urination due to enlargement of the prostate gland

Ask a doctor or pharmacist before use if you

are presently taking a prescription drug for high blood pressure or depression.

When using this product

do not exceed the recommended daily dosage unless directed by a doctor.

Stop use and ask a doctor if

■ condition worsens or does not improve within 7 days ■ bleeding occurs

■ introduction of applicator into the rectum causes additional pain

If pregnant or breast- feeding,

ask a health professional before use.

Keep out of reach of children.

If swallowed, get medical help or contact a Poison Control Center right away.

Directions

■ Adults: When practical, cleanse the affected area by patting or blotting with an appropriate cleansing pad. Gently dry by patting or blotting with toilet tissue or a soft cloth before applying ointment.
■ Apply to affected areas up to 4 times daily.
■ EXTERNAL USE: Apply to affected area
■ FOR INTRARECTAL USE: ■ Remove cover from the applicator ■ Attach applicator to tube ■ Lubricate applicator well, then gently insert applicator into the rectum ■ Thoroughly clean applicator after each use and replace cover
■ Children under 12 years of age: consult a doctor

Other information

■ Store at 15°C – 30°C (59°F – 86°F)
■ Lot No. & Expiry Date: See box or crimp of tube

Inactive ingredients

benzoic acid, butylated hydroxyanisole, corn oil, glycerin, lanolin, lanolin alcohols, methylparaben, mineral oil, paraffin, propylparaben, purified water, thyme oil, vitamin E, white wax

READ AND KEEP CARTON FOR COMPLETE INFORMATION

*This product is not manufactured or distributed by the owners of Preparation H® Hemorrhoidal Ointment.

Manufactured for: Bionpharma Inc., Princeton, NJ 08540

GUJ/DRUGS/G/25/2134

MADE IN INDIA

L0000812

R0424

LOT & EXP.

tube carton

*compare to the active ingredient in Preparation H® Hemorrhoid Treatment Ointment

NDC 69452-448-38

a+ healthTM

hemorrhoidal ointment

• reduces irritation • with applicator

dye-free • phthalate-free • fragrance-free

• relieves both internal and external hemorrhoid symptoms
• temporarily shrinks swollen hemorrhoidal tissue
• prompt, soothing relief from painful burning, itching and discomfort

net wt. 2 oz